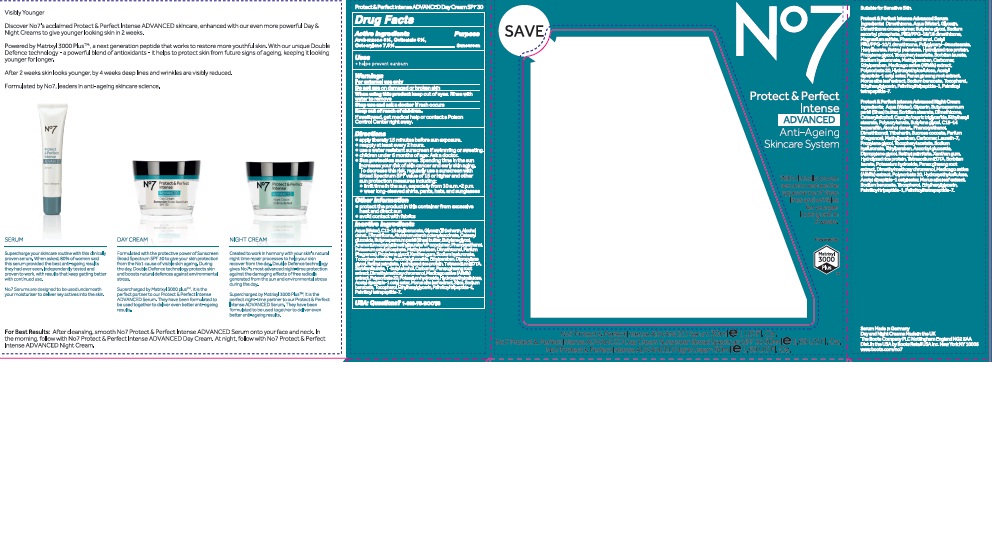 DRUG LABEL: No7 Protect and Perfect Intense Advanced Day Cream SPF 30
NDC: 11489-101 | Form: CREAM
Manufacturer: BCM Ltd
Category: otc | Type: HUMAN OTC DRUG LABEL
Date: 20160922

ACTIVE INGREDIENTS: AVOBENZONE 1.5 g/50 g; OCTOCRYLENE 3.75 g/50 g; OCTISALATE 2.5 g/50 g
INACTIVE INGREDIENTS: WATER; GLYCERIN; DIMETHICONE; CETEARYL GLUCOSIDE; ALUMINUM STARCH OCTENYLSUCCINATE; TRIBEHENIN; POTASSIUM CETYL PHOSPHATE; AMMONIUM ACRYLOYLDIMETHYLTAURATE/VP COPOLYMER; PHENOXYETHANOL; SHEA BUTTER; BUTYLENE GLYCOL; METHYLPARABEN; DIMETHICONOL (40 CST); PROPYLENE GLYCOL; DIPROPYLENE GLYCOL; XANTHAN GUM; ETHYLPARABEN; VITAMIN A PALMITATE; sodium; ASCORBYL GLUCOSIDE; MEDICAGO SATIVA LEAF; EDETATE SODIUM; TERT-BUTYL ALCOHOL; POLYSORBATE 20; CARBOMER 940; DIMETHYLMETHOXY CHROMANOL; POTASSIUM HYDROXIDE; ETHYLHEXYLGLYCERIN; PANAX GINSENG ROOT OIL; TOCOPHEROL; HYDROXYETHYL CELLULOSE (100 MPA.S AT 2%); MORUS ALBA LEAF; SILICON; PALMITOYL TETRAPEPTIDE-7; SODIUM BENZOATE; PALMITOYL TRIPEPTIDE-1

No7 Protect and Perfect Intense Advanced Day Cream Sunscreen Broad Spectrum SPF 30

Carton Active Ingredients Section

Active ingredients

Avobenzone 3%

Octisalate 5%

Octocrylene 7.50%

Uses

Uses - helps prevent sunburn

Warnings

For external use only

Do not use on damaged or broken skin

When using this product keep out of eyes. Rinse with water to remove.

Ask a doctor

Stop use and ask a doctor if rash occurs

Keep out of reach of children

If swallowed, get medical help or contact a Poison Control Center right away

Directions

Apply liberally 15 minutes before sun exposure

reapply at least every 2 hours

use a water resistant sunscreen if swimming or sweating

children under 6 months of age: Ask a doctor

Sun Protection Measures. Spending time in the sun increases your risk of skin cancer and early skin aging.

To decrease this risk, regularly use a sunscreen with a Broad Spectrum SPF value of 15 or higher and other sun protection measures including:

Limit time in the sun, especially from 10 a.m - 2 p.m.

wear long-sleeved shirts,pants,hats and sunglasses.

Storage

Other information

Protect the product in this container from excessive heat and direct sun

Avoid contact with fabrics

Inactive ingredients

Aqua(Water), C12-15 alkyl benzoate, Glycerin, Tribehenin, Alcohol denat., Dimethicone, Aluminum starch octenylsuccinate, Cetearyl glucoside, Butyrospermum parkii (Shea) butter, Butylene glycol, Ammonium acryloydimethyltaurate/VP copolymer, Phenoxyethanol, Potassium cetyl phosphate, Methylparaben, Dimethiconol, Parfum(Fragrance), Propylene glycol, Xanthan gum, Sodium hyaluronate, Tocopheryl acetate, Ascorbyl glucoside, Ethylparaben, Dipropylene glycol, Retinyl palmitate, hydolyzed rice protein, Tetrasodium EDTA, Sorbitan laurate, T-butyl alcohol, Carbomer, Panax gingseng root extract, Dimethylmethoxy chromanol, Medicago sativa (Alfalfa) extract, Polyosorbate 20, Potassium hydroxide, Hydroxyethylcelulose, Acetyl dipeptide-1 cetyl ester, Morus alba leaf extract, Silica, Sodium benzoate, Tocopherol, Ethylhexylglycerin, Palmitoyl tripeptide-1, Palmitoyl tetrapeptide-7.

PATIENT COUNSELING INFORMATION

Serum Made in Germany

Day and Night Creams Made in the UK

The Boots Company PLC Nottingham England NG2 3AA

Dist in the USA by Boots Retail USA Inc. New York NY 10005

www.boots.com/no7

Description

Visibly Younger

Discover No7's acclaimed Protect and Perfect Intense ADVANCED skincare, enhanced with our even more powerful Day and Night Creams to give younger looking skin in 2 weeks.

Powerd by Matrixyl 3000 Plus TM, a next generation peptide that works to restore more youthful skin. With our unique Double Defence technology - a powerful blend of antioxidants - it helps to protect skin from future signs of ageing, keeping it looking younger for longer.

After 2 weeks skin looks younger, by 4 weeks deep lines and wrinkles are visibly reduced.

Formulated by No7, leaders in anti-ageing skincare science.

SERUM

Supercharge your skincare routine with this clinically proven serum. When asked, 80% of women said this serum provided the best anti-ageing results they had ever seen. Independently tested and proven to work, with results that keep getting better with continued use.

No7 Serums are designed to be used underneath your moisturiser to deliver key actives into the skin.

DAY CREAM

Formulated with the protective power of Sunscreen Broad Spectrum SPF 30 to give your skin protection from the No1 cause of visible skin ageing. During the day, double Defence technology protects skin and boosts natural defences against environmental stress.

Supercharged by Matrixyl 3000 plus TM, it is the perfect partner to our Protect and Perfect Intense Advanced Serum. They have been formulated to be used together to deliver even better anti-ageing results.

NIGHT CREAM

Created to work in harmony with your skin's natural night time repair processes to help your skin recover from the day. Double Defence technology gives No7's most advanced night-time protction against the damaging effects of free radicals generated from the sun and environmental stress during the day.

Supercharged by Matrixyl 3000 Plus TM, it is the perfect night-time partner to our Protect and Perfect Intense ADVANCED Serum. They have been formulated to be used together to deliver even better anti-ageing results.

For Best Results: After cleansing, smooth No7 Protect and Perfect Intense ADVANCED Serum onto your face and neck. In the morning, follow with No7 Protect and Perfect Intense ADVANCED Day Cream. At night, follow with No7 Protect and Perfect Intense ADVANCED Night Cream.